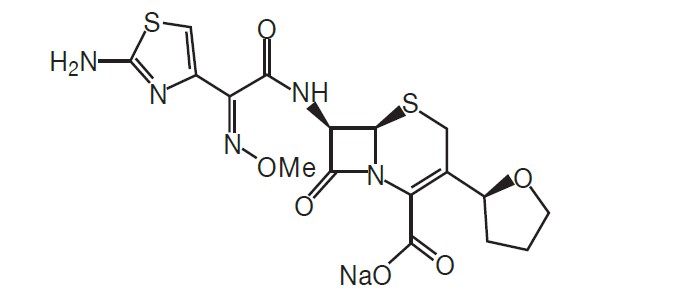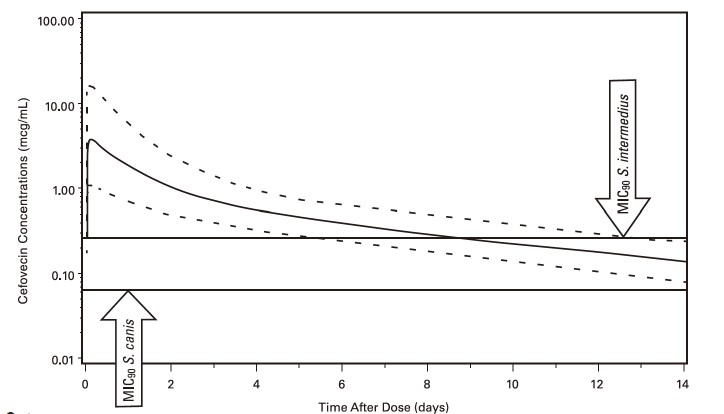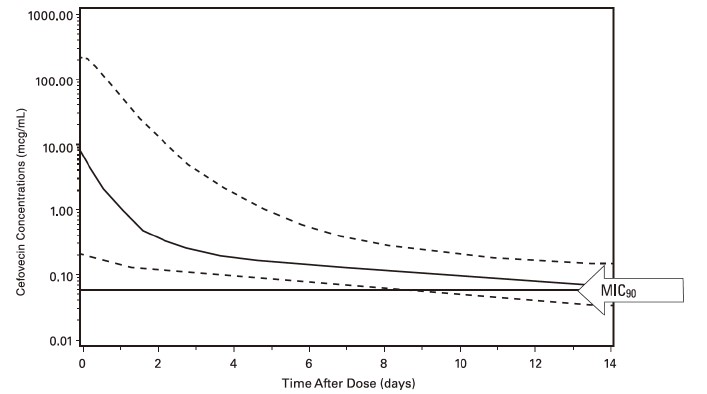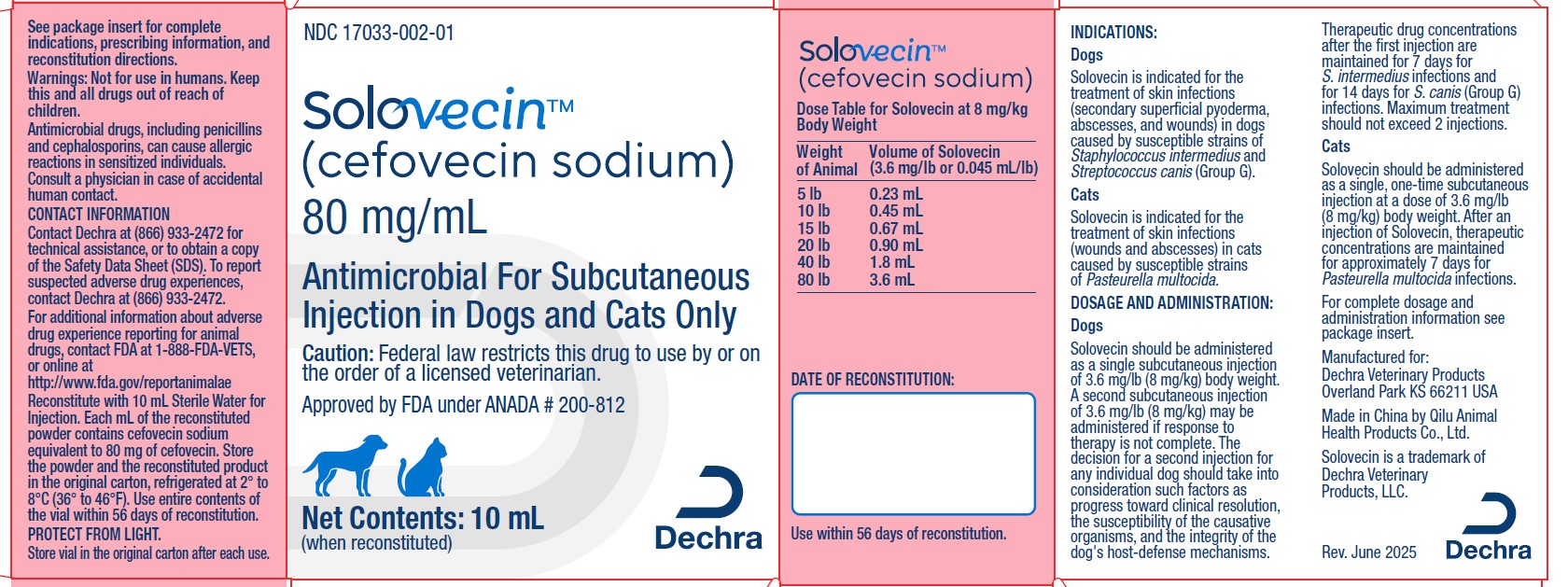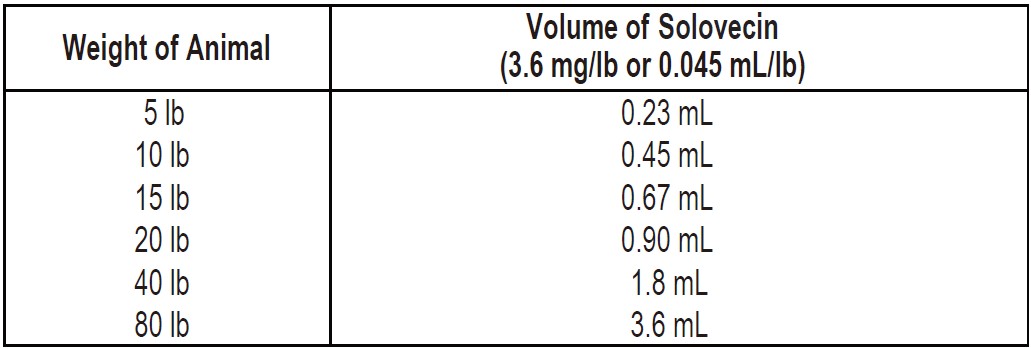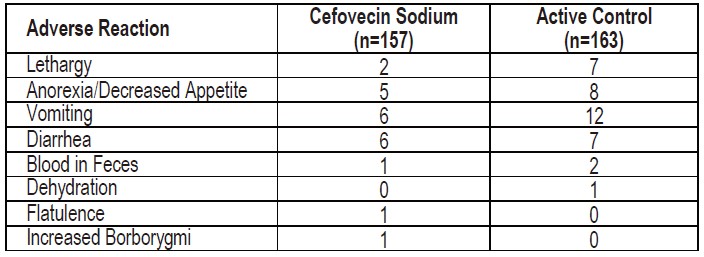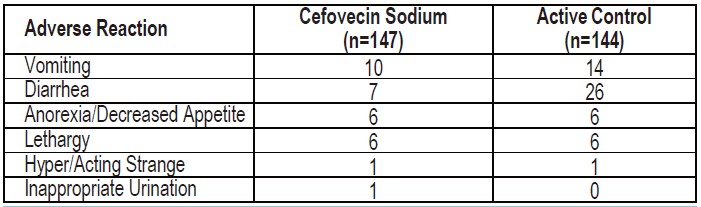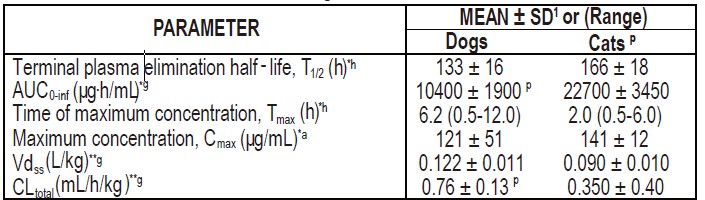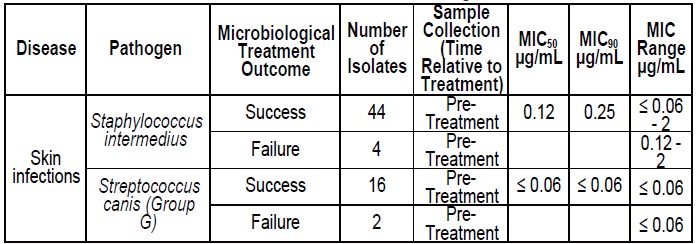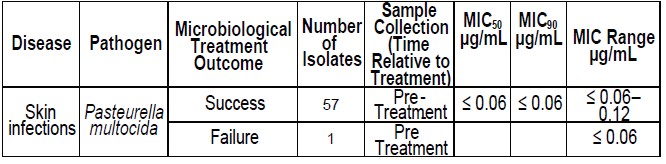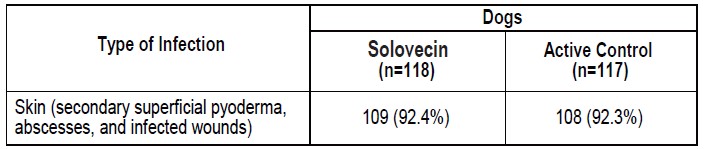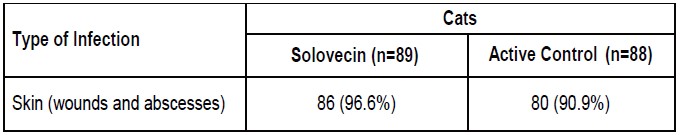 DRUG LABEL: Solovecin
NDC: 17033-002 | Form: INJECTION, POWDER, LYOPHILIZED, FOR SOLUTION
Manufacturer: Dechra Veterinary Products, LLC
Category: animal | Type: PRESCRIPTION ANIMAL DRUG LABEL
Date: 20250903

ACTIVE INGREDIENTS: Cefovecin Sodium 80 mg/1 mL

Solovecin™
(cefovecin sodium)

Antimicrobial for Subcutaneous Injection in Dogs and Cats Only

CAUTION: Federal law restricts this drug to use by or on the order of a licensed veterinarian.

DESCRIPTION

DESCRIPTION: Cefovecin sodium is a semi-synthetic broad-spectrum antibacterial agent from the cephalosporin class of chemotherapeutic agents. Cefovecin is the non-proprietary designation for (6R,7R)-7-[[(2Z)-(2-amino-4-thiazolyl)(methoxyimino)acetyl]amino]-8-oxo-3-[(2S)tetrahydro-2-furanyl]-5-thia-1-azabicyclo[4.2.0]oct-2-ene-2-carboxylic acid, monosodium salt.

Figure 1: Chemical structure of cefovecin sodium.

Each mL of Solovecin reconstituted lyophile contains cefovecin sodium equivalent to 80.0 mg cefovecin, methylparaben 1.8 mg (preservative), propylparaben 0.2 mg (preservative), sodium citrate dihydrate 5.8 mg and citric acid monohydrate 0.1 mg, sodium hydroxide or hydrochloric acid as required to adjust pH.

INDICATIONS:

Dogs
Solovecin is indicated for the treatment of skin infections (secondary superficial pyoderma, abscesses, and wounds) in dogs caused by susceptible strains of Staphylococcus intermedius and Streptococcus canis (Group G).

Cats
Solovecin is indicated for the treatment of skin infections (wounds and abscesses) in cats caused by susceptible strains of Pasteurella multocida.

DOSAGE AND ADMINISTRATION:

Dogs

Solovecin should be administered as a single subcutaneous injection of 3.6 mg/lb (8 mg/kg) body weight. A second subcutaneous injection of 3.6 mg/lb (8 mg/kg) may be administered if response to therapy is not complete. The decision for a second injection for any individual dog should take into consideration such factors as progress toward clinical resolution, the susceptibility of the causative organisms, and the integrity of the dog's host-defense mechanisms. Therapeutic drug concentrations after the first injection are maintained for 7 days for S. intermedius infections and for 14 days for S. canis (Group G) infections. Maximum treatment should not exceed 2 injections.

Cats

Solovecin should be administered as a single, one-time subcutaneous injection at a dose of 3.6 mg/lb (8 mg/kg) body weight. After an injection of Solovecin, therapeutic concentrations are maintained for approximately 7 days for Pasteurella multocida infections.

General Dosing Information
A sample of the lesion should be obtained for culture and susceptibility testing prior to beginning antimicrobial therapy. Once results become available, continue with appropriate therapy. If acceptable response to treatment is not observed, or if no improvement is seen within 3 to 4 days, then the diagnosis should be re-evaluated and appropriate alternative therapy considered. Solovecin may persist in the body for up to 65 days. The effect of remaining concentrations of cefovecin on any subsequent antimicrobial therapies has not been determined. Fluoroquinolone and aminoglycoside antimicrobials have been reported to be compatible with cephalosporin antimicrobial agents.1,2,3

Table 1: Dose Table for Solovecin at 8 mg/kg Body Weight

PREPARATION OF SOLUTION FOR INJECTION: To deliver the appropriate dose, aseptically reconstitute Solovecin with 10 mL Sterile Water for Injection. Shake and allow vial to sit until all material is visually dissolved. The resulting solution contains cefovecin sodium equivalent to 80 mg/mL cefovecin. Solovecin is light sensitive. The vial should be stored in the original carton and refrigerated when not in use. Use the entire contents of the vial within 56 days of reconstitution.

CONTRAINDICATIONS

CONTRAINDICATIONS: Solovecin is contraindicated in dogs and cats with known allergy to cefovecin or to β-lactam (penicillins and cephalosporins) group antimicrobials. Anaphylaxis has been reported with the use of this product in foreign market experience. If an allergic reaction or anaphylaxis occurs, Solovecin should not be administered again and appropriate therapy should be instituted. Anaphylaxis may require treatment with epinephrine and other emergency measures, including oxygen, intravenous fluids, intravenous antihistamine, corticosteroids, and airway management, as clinically indicated. Adverse reactions may require prolonged treatment due to the prolonged systemic drug clearance (65 days).

WARNINGS

WARNINGS: Not for use in humans. Keep this and all drugs out of reach of children.
Consult a physician in case of accidental human exposure. For subcutaneous use in dogs and cats only. Antimicrobial drugs, including penicillins and cephalosporins, can cause allergic reactions in sensitized individuals. To minimize the possibility of allergic reactions, those handling such antimicrobials, including cefovecin, are advised to avoid direct contact of the product with the skin and mucous membranes.

PRECAUTIONS:

Prescribing antibacterial drugs in the absence of a proven or strongly suspected bacterial infection is unlikely to provide benefit to treated animals and may increase the risk of the development of drug-resistant animal pathogens.

The safe use of Solovecin in dogs or cats less than 4 months of age (see Animal Safety) and in breeding or lactating animals has not been determined. Safety has not been established for IM or IV administration. The long-term effects on injection sites have not been determined. Solovecin is slowly eliminated from the body, approximately 65 days is needed to eliminate 97% of the administered dose from the body. Animals experiencing an adverse reaction may need to be monitored for this duration.

Solovecin has been shown in an experimental in vitro system to result in an increase in free concentrations of carprofen, furosemide, doxycycline and ketoconazole. Concurrent use of these or other drugs that have a high degree of protein-binding (e.g. NSAIDs, propofol, cardiac, anticonvulsant, and behavioral medications) may compete with cefovecin binding and cause adverse reactions.

Positive direct Coombs' test results and false positive reactions for glucose in the urine have been reported during treatment with some cephalosporin antimicrobials. Cephalosporin antimicrobials may also cause falsely elevated urine protein determinations. Some antimicrobials, including cephalosporins, can cause lowered albumin values due to interference with certain testing methods.

Occasionally, cephalosporins and NSAIDs have been associated with myelotoxicity, thereby creating a toxic neutropenia4. Other hematological reactions seen with cephalosporins include neutropenia, anemia, hypoprothrombinemia, thrombocytopenia, prolonged prothrombin time (PT) and partial thromboplastin time (PTT), platelet dysfunction and transient increases in serum aminotransferases.

ADVERSE REACTIONS:

Dogs

A total of 320 dogs, ranging in age from 8 weeks to 19 years, were included in a field study safety analysis. Adverse reactions reported in dogs treated with cefovecin sodium and the active control are summarized in Table 2.

Table 2: Number of Dogs* with Adverse Reactions Reported During the Field Study with Cefovecin Sodium

* Some dogs may have experienced more than one adverse reaction or more than one occurrence of the same adverse reaction during the study.

Mild to moderate elevations in serum gamma glutamyl transferase or serum alanine aminotransferase were noted post-treatment in several of the CEFOVECIN-treated dogs. No clinical abnormalities were noted with these findings.

One cefovecin sodium-treated dog in a separate field study experienced diarrhea post-treatment lasting four weeks. The diarrhea resolved.

Cats

A total of 291 cats, ranging in age from 2.4 months (one cat) to 21 years, were included in the field study safety analysis. Adverse reactions reported in cats treated with cefovecin sodium and the active control are summarized in Table 3.

Table 3: Number of Cats* with Adverse Reactions Reported During the Field Study with Cefovecin Sodium.

* Some cats may have experienced more than one adverse reaction or more than one occurrence of the same adverse reaction during the study.

Four cefovecin sodium cases had mildly elevated post-study ALT (one case was elevated pre-study). No clinical abnormalities were noted with these findings.

Twenty-four cefovecin sodium cases had normal pre-study BUN values and elevated post-study BUN values (37 – 39 mg/dL post-study). There were 6 cefovecin sodium cases with normal pre- and mildly to moderately elevated post-study creatinine values. Two of these cases also had an elevated post-study BUN. No clinical abnormalities were noted with these findings.

One cefovecin sodium-treated cat in a separate field study experienced diarrhea post-treatment lasting 42 days. The diarrhea resolved.

FOREIGN MARKET EXPERIENCE: The following adverse events were reported voluntarily during post-approval use of the product in dogs and cats in foreign markets: death, tremors/ataxia, seizures, anaphylaxis, acute pulmonary edema, facial edema, injection site reactions (alopecia, scabs, necrosis, and erythema), hemolytic anemia, salivation, pruritus, lethargy, vomiting, diarrhea, and inappetance.

CONTACT INFORMATION: To report suspected adverse reactions, to obtain a Safety Data Sheet (SDS), or for technical assistance, contact Dechra Veterinary Products at 1-866-933-2472.

For additional information about adverse drug experience reporting for animal drugs, contact FDA at 1-888-FDA-VETS or http://www.fda.gov/reportanimalae

CLINICAL PHARMACOLOGY:

Pharmacokinetics

Cefovecin is rapidly and completely absorbed following subcutaneous administration. Non-linear kinetics is exhibited (plasma concentrations do not increase proportionally with dose). Cefovecin does not undergo hepatic metabolism and the majority of a dose is excreted unchanged in the urine. Elimination also occurs from excretion of unchanged drug in the bile. Cefovecin is a highly protein bound molecule in dog plasma (98.5%) and cat plasma (99.8%) and may compete with other highly protein bound drugs for plasma protein binding sites that could result in transient, higher free drug concentrations of either compound. Pharmacokinetic parameters following subcutaneous dosing at 8 mg/kg in the dog and cat
are summarized in Table 4.

Table 4: Pharmacokinetic Parameters Reflecting Total Drug Concentrations in Plasma (mean ± standard deviation or range) Following an 8 mg/kg Intravenous or Subcutaneous Dose of Cefovecin in Dogs and Cats

^1SD = standard deviation
p= a phase effect was observed, only data for the first phase are provided (n=6); all other data
provided are derived from 12 animals
*= SC
**= IV
a= arithmetic mean
h= harmonic mean
g= geometric mean

Population Pharmacokinetics

Dogs

Cefovecin plasma concentrations in the dog have been characterized by the use of population pharmacokinetic (PPK) data. Plasma cefovecin concentration data were pooled from seven laboratory pharmacokinetic studies, each involving young, normal healthy Beagle
dogs. The final dataset contained 591 concentration records from 39 dogs. The simulations from the model provide the mean population estimate and the 5th and 95th percentile of the population estimates of total and free cefovecin concentrations over time. Figure 2 shows the predicted free plasma concentrations following administration of 8 mg/kg body weight to dogs. Based upon these predicted concentrations, 95% of the canine population will have active (free) drug concentrations > the MIC90 of S. canis (0.06 μg/mL) for approximately 14 days and free concentrations > the MIC90 for S. intermedius (0.25 μg/mL) for approximately 7 days following a single 8 mg/kg subcutaneous injection of cefovecin. (See MICROBIOLOGY.)

Figure 2: Population Predicted Free Concentration of Cefovecin in Plasma Following a Single Subcutaneous Injection of 8 mg/kg Body Weight in Dogs (solid line is population prediction, dotted lines are the 5th and 95th percentiles for the population prediction).

Cats

Cefovecin plasma concentrations in the cat have been characterized by the use of PPK data. Plasma cefovecin concentration data were pooled from four laboratory pharmacokinetic studies. The final dataset contained 338 concentration records from 22 cats. The simulations from the model provide the mean population estimate as well as the 5th and 95th percentile of the population estimates of total and free cefovecin concentrations over time. Figure 3 displays the predicted free plasma concentrations following administration of 8 mg/kg body weight to cats. Based upon these predicted concentrations, 95% of the feline population will have active (free) drug concentrations > the MIC90 of Pasteurella multocida (0.06 μg/mL) for approximately 7 days when administered a single 8 mg/kg subcutaneous injection of cefovecin. (See MICROBIOLOGY.)

Figure 3: Population Predicted Free Concentration of Cefovecin in Plasma Following a Single Subcutaneous Injection of 8 mg/kg Body Weight in Cats (solid line is population prediction, dotted lines are the 5th and 95th percentiles for the population prediction).

MICROBIOLOGY

MICROBIOLOGY: Cefovecin sodium is a cephalosporin antibiotic. Like other β-lactam antimicrobials, cefovecin sodium exerts its inhibitory effect by interfering with bacterial cell wall synthesis. This interference is primarily due to its covalent binding to the penicillin-binding proteins (PBPs (i.e., transpeptidase and carboxypeptidase), which are essential for synthesis of the bacterial cell wall. For E. coli, the in vitro activity of cefovecin sodium is comparable to other cephalosporins, but due to the high-affinity protein-binding, the in vivo free concentration of cefovecin does not reach the MIC90 for E. coli (1.0 μg/mL). Cefovecin sodium is not active against Pseudomonas spp. or enterococci.

Dogs

The minimum inhibitory concentration (MIC) values for cefovecin against label-claim pathogens isolated from skin infections in dogs enrolled in a 2001-2003 field effectiveness study are presented in Table 5. All MICs were determined in accordance with the Clinical and Laboratory Standards Institute (CLSI) standards.

Table 5. Activity of Cefovecin Sodium Against Pathogens Isolated from Dogs Treated With Cefovecin Sodium in Field Studies in the U.S. During 2001-2003.

Cats

The MIC values for cefovecin against Pasteurella multocida isolated from skin infections (wounds and abscesses) in cats enrolled in a 2001-2003 field effectiveness study are presented in Table 6. All MICs were determined in accordance with the CLSI standards.

Table 6. Activity of Cefovecin Sodium Against Pathogens Isolated from Cats Treated With Cefovecin Sodium in Field Studies in the U.S. During 2001-2003.

SUMMARY OF SAFETY AND EFFECTIVENESS

EFFECTIVENESS:

Dogs

In a double-masked, 1:1 randomized canine field study conducted in the United States, the effectiveness of cefovecin sodium was compared to a cephalosporin active control. In this study, 320 dogs with superficial secondary pyoderma, abscesses, or infected wounds were treated with either a single injection of cefovecin sodium (n = 157) at 3.6 mg/lb (8 mg/kg) body weight or with an oral active control antibiotic (n = 163), administered twice daily for 14 days. In this study, dogs could receive a second course of therapy 14 days after the initial treatment. Of the 320 enrolled dogs, 22 of 157 dogs received two treatments of cefovecin sodium and 35 of 163 dogs received two courses of treatment with the active control. In the study, 118 of the 157 enrolled cases were evaluable for effectiveness for cefovecin sodium, and 117 of the 163 enrolled cases were evaluable for effectiveness of the active control antibiotic. Cefovecin sodium was non-inferior to the active control. Table 7 summarizes the clinical success rates obtained 28 days after the initiation of the final course of therapy.

Table 7: Clinical Success Rates by Treatment Group 28 Days after the Initiation of the Final Course of Therapy.

Cefovecin sodium was administered concomitantly with other commonly used veterinary products such as heartworm preventatives, flea control products, sedatives/tranquilizers, anesthetic agents, routine immunizations, antihistamines, thyroid hormone supplementation, and non-steroidal anti-inflammatory drugs during the field study.

Cats

In a double-masked, 1:1 randomized cat field study conducted in the United States, the effectiveness of cefovecin sodium was compared to an active control. In this study, 291 cats with infected wounds or abscesses were treated with either a single injection of cefovecin sodium (n = 147) at 3.6 mg/lb (8 mg/kg) body weight or with an oral active control antibiotic (n = 144), administered once daily for 14 days. Cefovecin sodium was non-inferior to the active control. The clinical success rates were obtained 28 days after the initiation of therapy and are presented in Table 8.

Table 8: Clinical Success Rates by Treatment Group 28 Days after the Initiation of Therapy.

Cefovecin sodium was used concomitantly with other commonly used veterinary products such as heartworm preventatives, flea control products, sedatives/tranquilizers, anesthetic agents, and vaccines during the field study.

ANIMAL SAFETY:

Dogs

Cefovecin sodium administered to healthy four month old dogs at doses of 12 mg/kg (1.5X), 36 mg/kg (4.5X), and 60 mg/kg (7.5X) every seven days by dorsoscapular subcutaneous injections was well-tolerated for a total of 5 doses. Vomiting and diarrhea were seen in all treatment groups, with the incidence of vomiting and the incidence and duration of diarrhea increasing in a dose-related manner. Injection site irritation and transient edema occurred with increasing frequency in a dose-related manner and with repeat injections. Two injection site reactions included a seroma over the shoulder and swelling lasting > 30 days. Dogs dosed at 36 mg/kg had a significant (p = 0.0088) increase in BUN (all means remained within the normal range) compared to the controls. One dog dosed at 60 mg/kg exhibited a glomerulopathy on histopathology, and one dog in this same group had minimal peliosis hepatis.

At an exaggerated dose of 180 mg/kg (22.5X) in dogs, cefovecin sodium caused some injection site irritation, vocalization and edema. Edema resolved within 8-24 hours.

Cats

Cefovecin sodium administered to healthy four month old cats at doses of 12 mg/kg (1.5X), 36 mg/kg (4.5X), and 60 mg/kg (7.5X) every seven days by dorsoscapular subcutaneous injections was well tolerated for a total of 5 doses. Vomiting and diarrhea were observed in cats, with the incidence of vomiting, and the incidence and duration of diarrhea increasing in a dose-related manner. The mean albumin values for all the cefovecin sodium-treated cats were significantly lower (p ≤ 0.05) than the control values (all means remained within the normal range) for all time periods. The mean alkaline phosphatase values in the 60 mg/kg group were significantly higher (p ≤ 0.0291) than the control values for all time periods. Injection-site irritation and transient edema occurred with increasing frequency in a dose-related manner and with repeat injections. One cat in the 12 mg/kg group had a mild renal tubular and interstitial fibrosis, and one cat in the 12 mg/kg group had mild glomerulosclerosis on histopathology.

At an exaggerated dose of 180 mg/kg (22.5X), cefovecin sodium was associated with injection site irritation, vocalization and edema. Edema resolved within 8-24 hours. On Day 10, cats had lower mean white blood cell counts compared to the controls. One cat had a small amount of bilirubinuria on Day 10.

STORAGE INFORMATION:

Store the powder and the reconstituted product in the original carton, refrigerated at 2° to 8° C (36° to 46° F). Use the entire contents of the vial within 56 days of reconstitution. PROTECT FROM LIGHT. After each use it is important to return the unused portion back to the refrigerator in the original carton. As with other cephalosporins, the color of the solution may vary from clear to amber at reconstitution and may darken over time. If stored as recommended, solution color does not adversely affect potency.

HOW SUPPLIED

Solovecin is available as a 10 mL multi-use vial containing 800 milligrams of cefovecin as a lyophilized cake.

REFERENCES

^1Pillai SK, Moellering RC, and Eliopoulos GM. 2005. Antimicrobial combinations, pp 365-440. In V. Lorian (ed.) Antibiotics in Laboratory Medicine, 5th ed., Lippincott, Williams, and Wilkins, Philadelphia, PA.

^2Fish DN, Choi MK, and Jung R: Synergic activity of cephalosporins plus fluoroquinolones against Pseudomonas aeruginosa with resistance to one or both drugs. Journal of Antimicrobial Chemotherapy (2002) 50, 1045–1049.

^3Mayer I and Nagy E: Investigation of the synergic effects of aminoglycoside-fluoroquinolone and third-generation cephalosporin combinations against clinical isolates of Pseudomonas spp. Journal of Antimicrobial Chemotherapy (1999) 43, 651–657.

^4Birchard SJ and Sherding RG. Saunders Manual of Small Animal Practice, 2nd edition. W.B. Saunders Co. 2000: p. 166.

Approved by FDA under ANADA # 200-812

Manufactured for:
Dechra Veterinary Products
Overland Park, KS 66211 USA

Made in China by Qilu Animal Health Products Co., Ltd.

Solovecin is a trademark of Dechra Veterinary Products, LLC.

Rev. June 2025

PRINCIPAL DISPLAY PANEL - 10 mL Vial Carton

NDC 17033-002-01

Solovecin™
(cefovecin sodium)

80 mg/mL

Antimicrobial For Subcutaneous
Injection in Dogs and Cats Only

Caution: Federal law restricts this drug to use by or on
the order of a licensed veterinarian.

Approved by FDA under ANADA # 200-812

Net Contents: 10 mL (when reconstituted)

Dechra